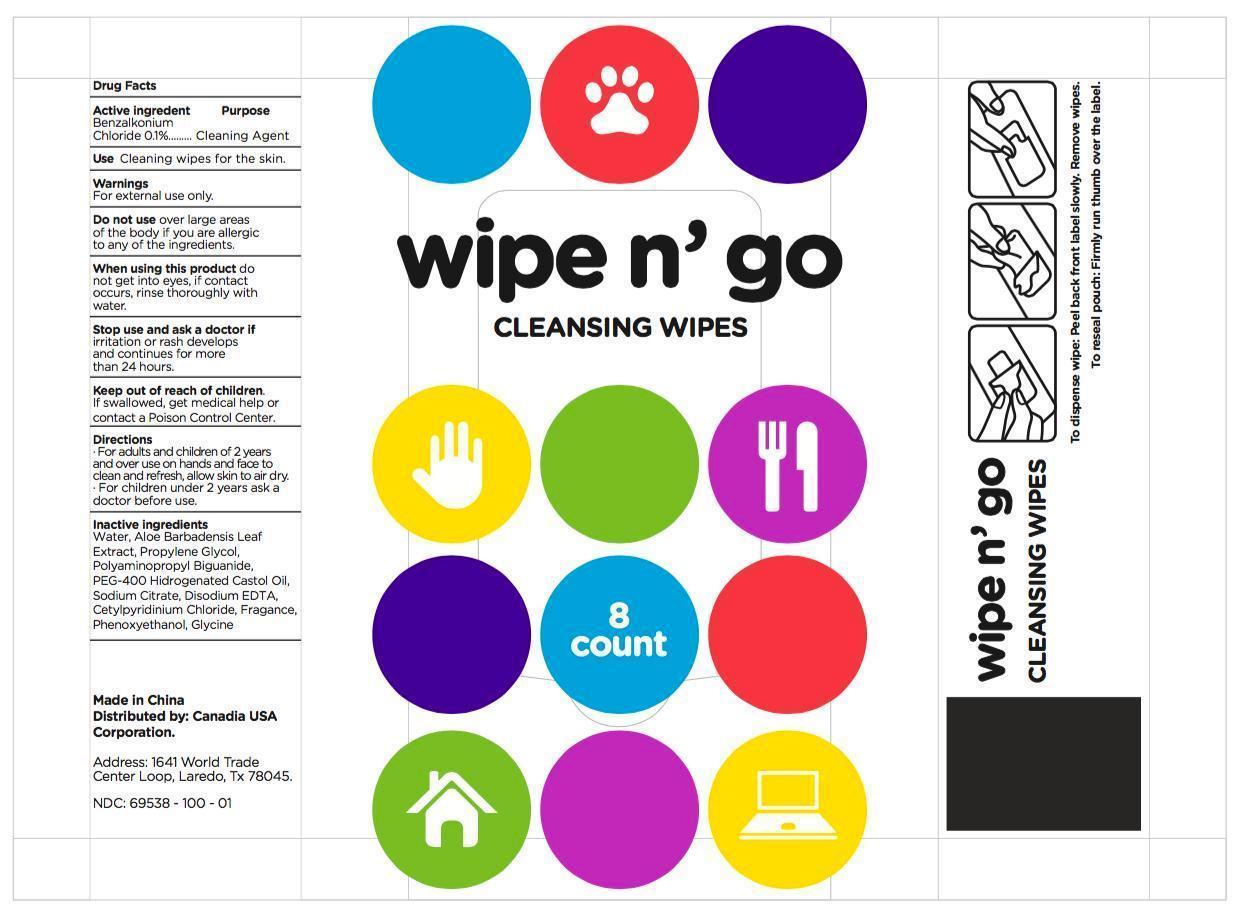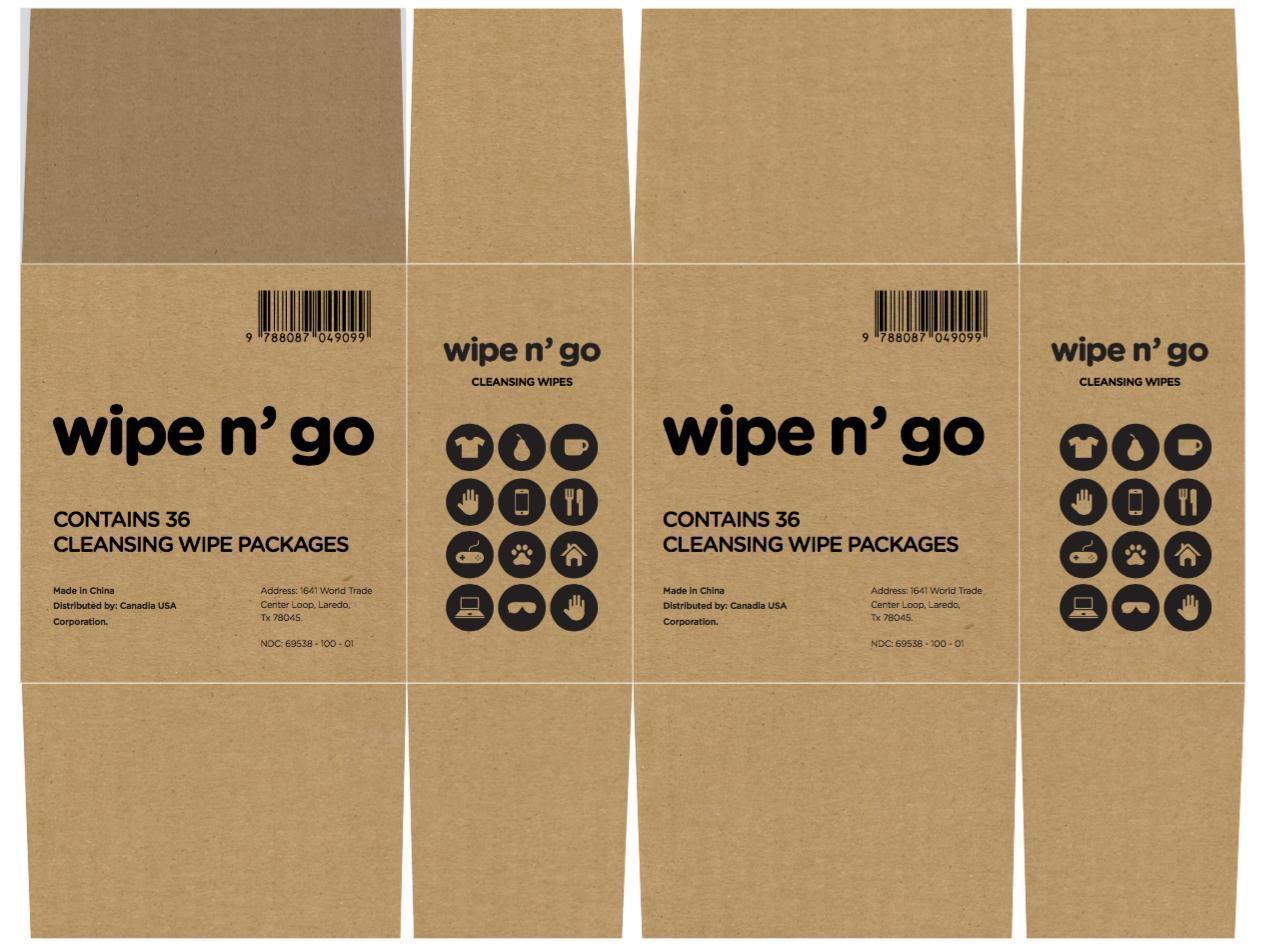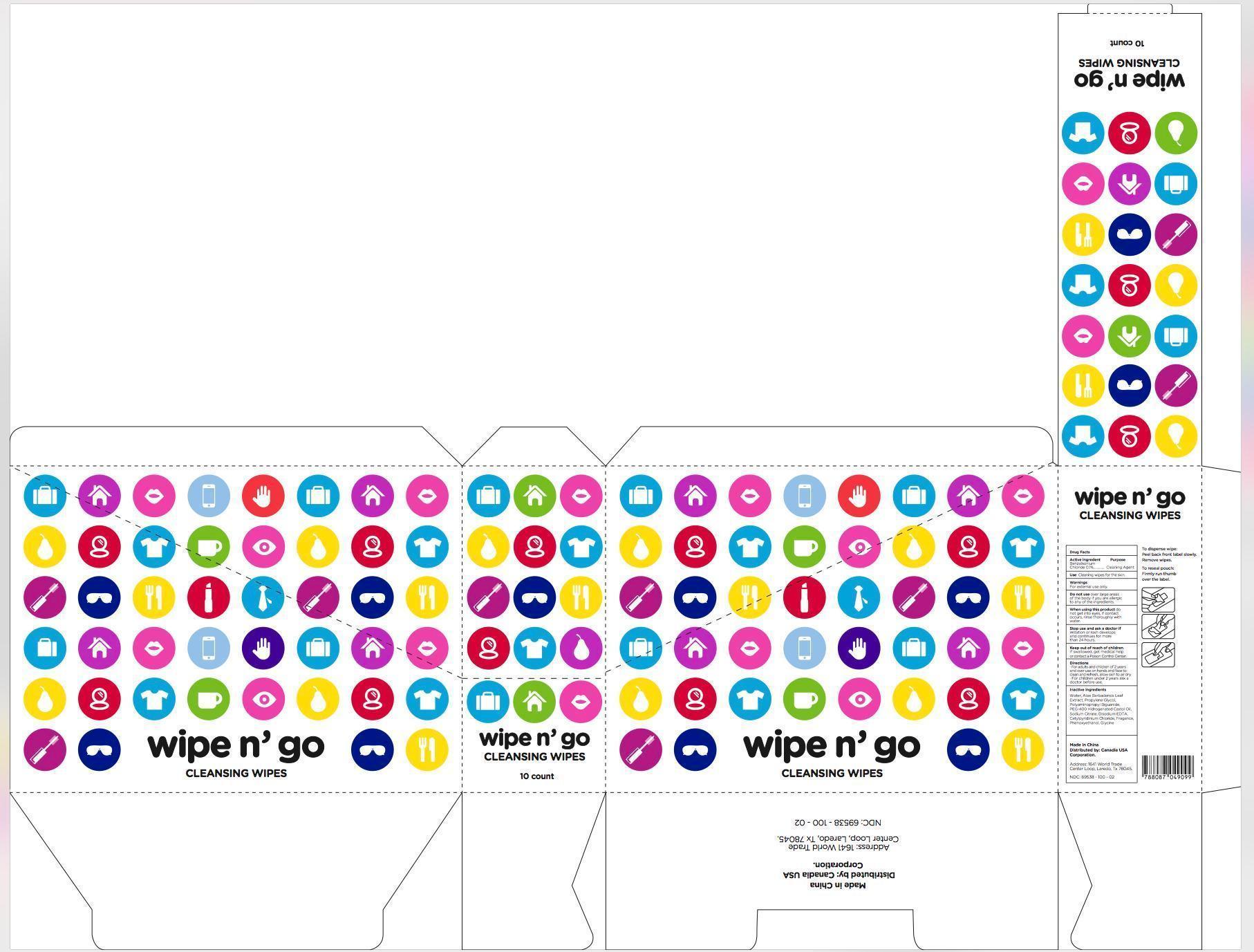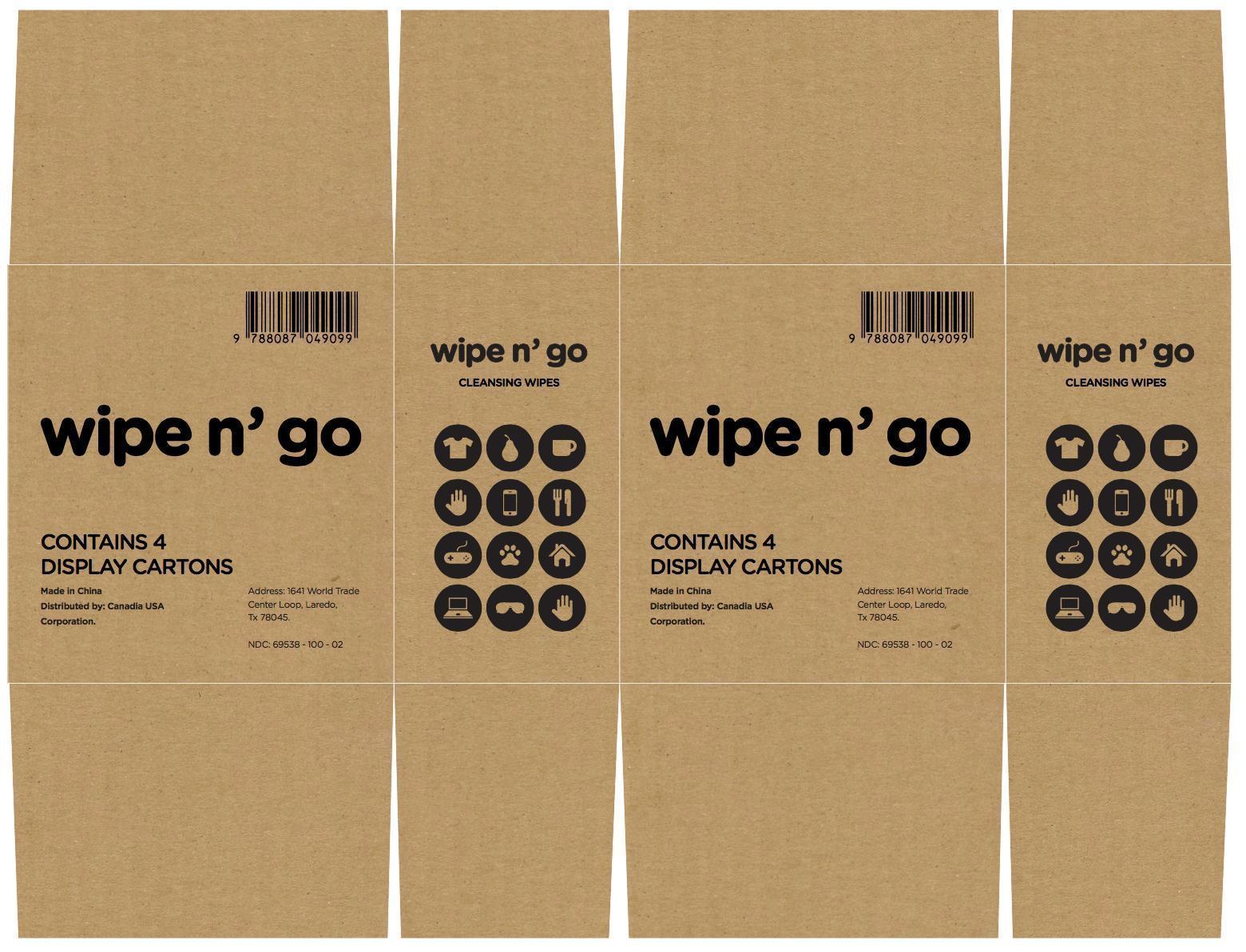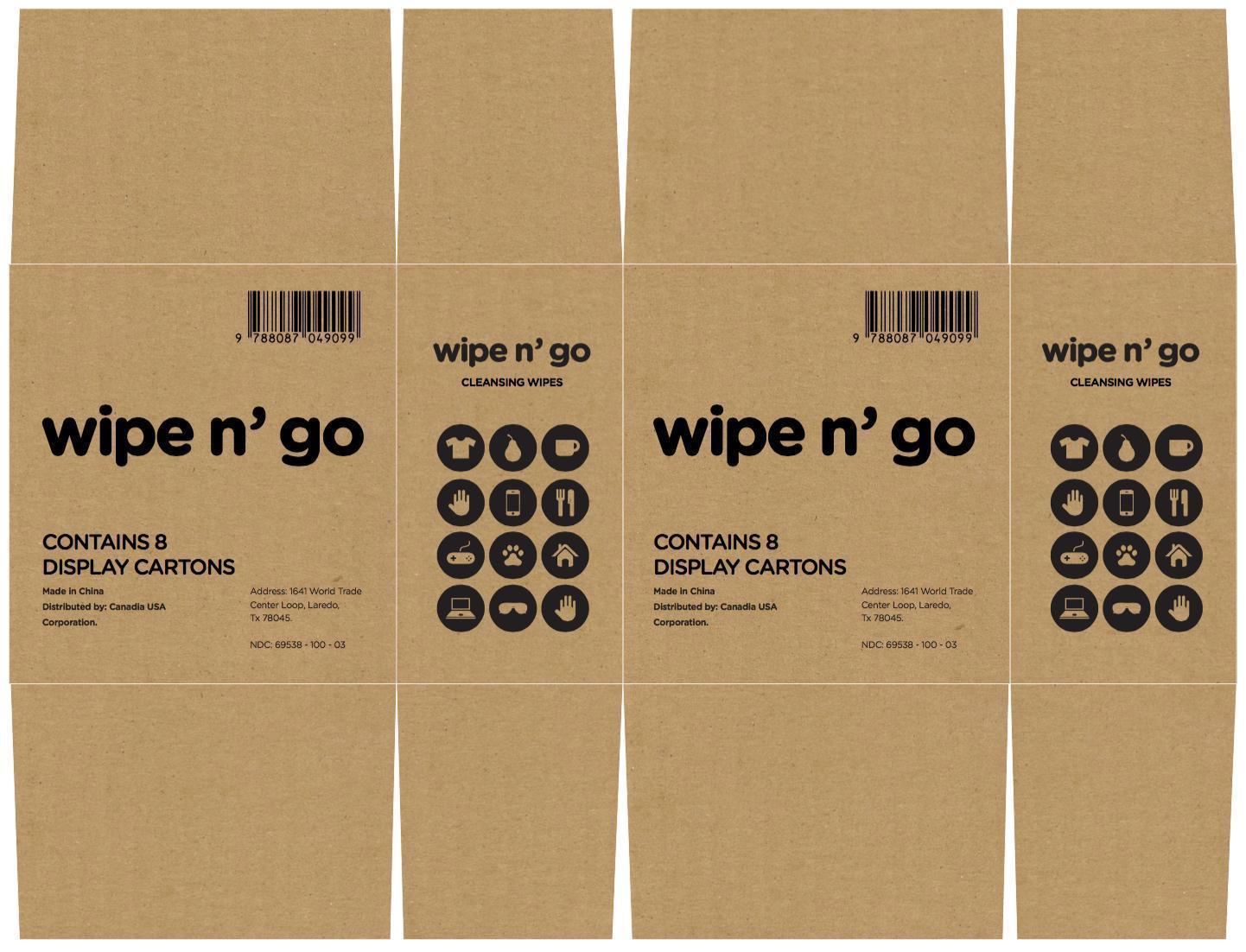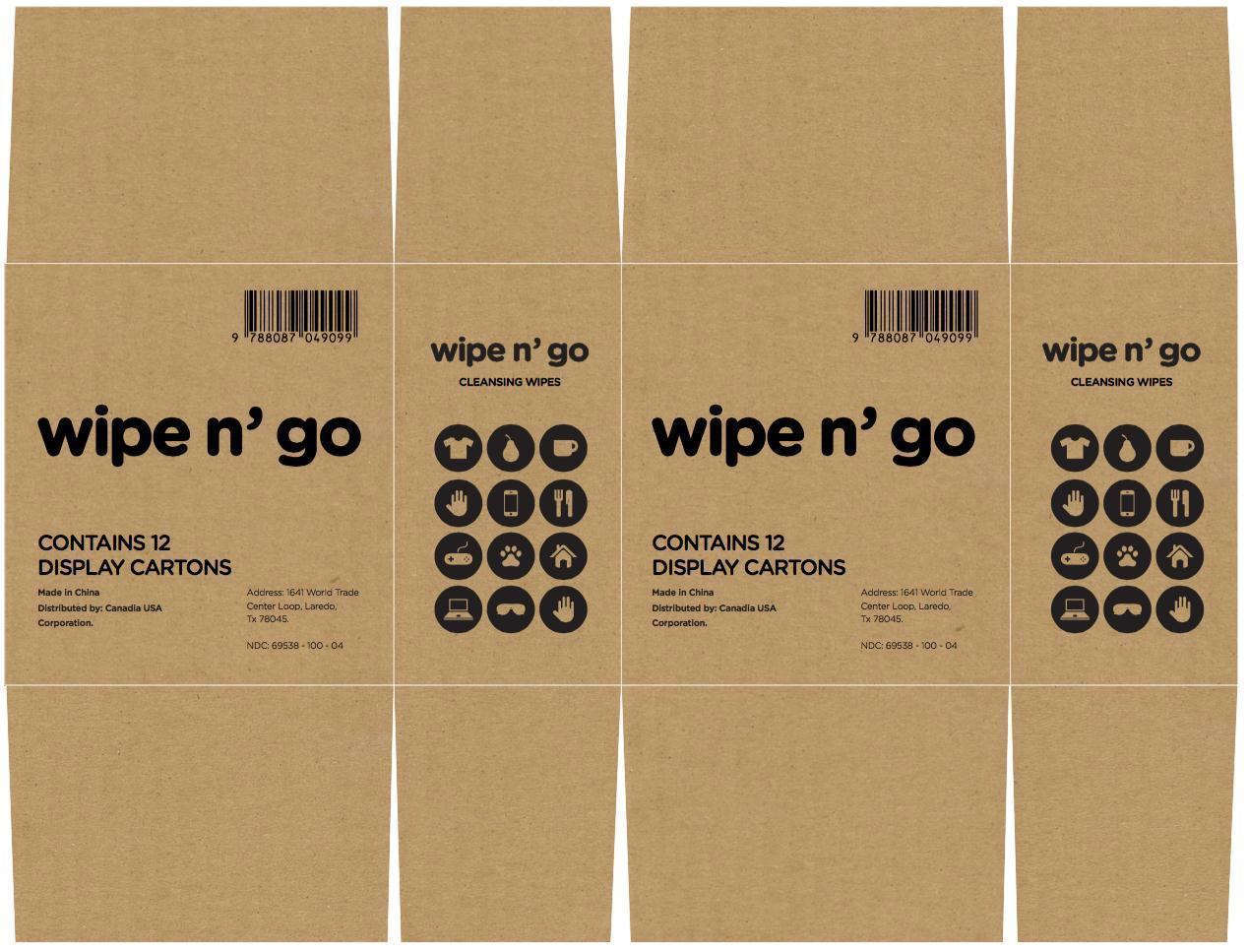 DRUG LABEL: Wipe n Go
NDC: 69538-100 | Form: SWAB
Manufacturer: CANADIA USA CORPORATION
Category: otc | Type: HUMAN OTC DRUG LABEL
Date: 20150821

ACTIVE INGREDIENTS: BENZALKONIUM CHLORIDE 0.13 g/100 g
INACTIVE INGREDIENTS: WATER; ALOE VERA LEAF; PROPYLENE GLYCOL; POLIHEXANIDE; HYDROGENATED CASTOR OIL; SODIUM CITRATE; EDETATE DISODIUM; CETYLPYRIDINIUM; PHENOXYETHANOL; GLYCINE

Drug Facts

Active ingredient

Benzalkonium Chloride, 0.1%

Purpose

Cleaning Agent

Uses

Cleaning wipes for the skin.

Warnings:

For external use only.

Do not

over large areas of the body if you are allergic to any of the ingredients.

When using this product

do not get into eyes, if contact occurs, rinse thoroughly with water.

Stop use and ask a doctor if

irritation or rash develops and continues for more than 24 hours.

Keep out of reach of children

If swallowed, get medical help or contact a Poison Control Center right away.

Directions:

For adults and children of 2 years and over, use on hands and face to clean and refresh, allow skin to air dry.

For children under 2 years, ask a doctor before use.

Inactive ingredients:

Water, Aloe Barbadensis Leaf Extract, Propylene Glycol, Polyaminopropyl Biguanide, PEG-400 Hydrogenated Castor Oil, Sodium Citrate, Disodium EDTA, Cetylpyridinium Chloride, Fragrance, Phenoxyethanol, Glycine

Principal Display Panel

wipe n' go

CLEANSING WIPES

Made in China

Distributed by: Canadia USA Corporation.